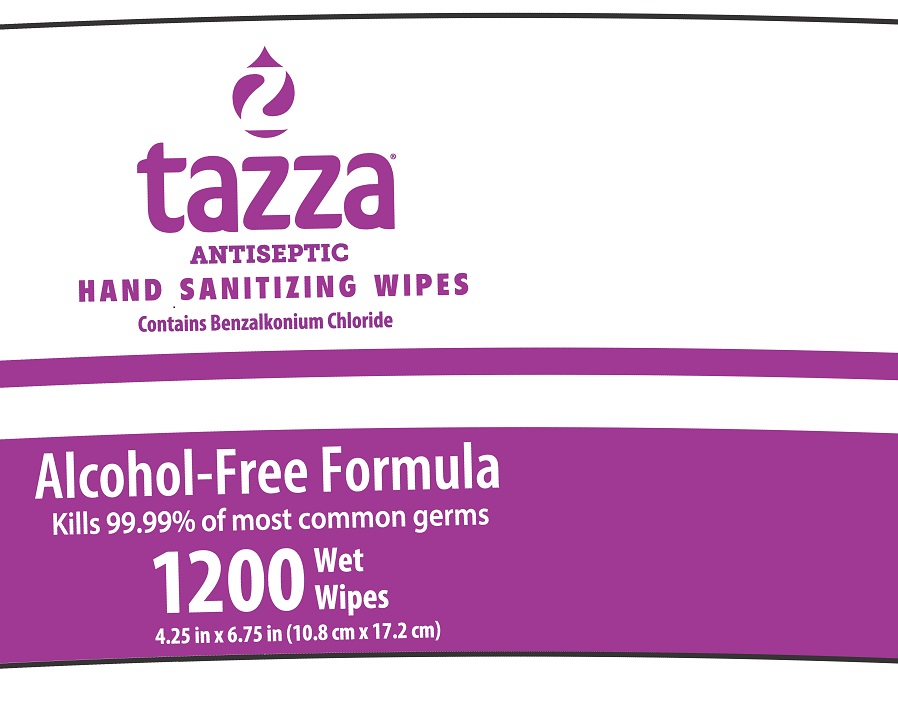 DRUG LABEL: Tazza
NDC: 76370-0009 | Form: CLOTH
Manufacturer: Tazza Brands East Inc.
Category: otc | Type: HUMAN OTC DRUG LABEL
Date: 20240124

ACTIVE INGREDIENTS: BENZALKONIUM CHLORIDE 0.13 g/100 mL
INACTIVE INGREDIENTS: WATER; GLYCERIN; ALOE VERA LEAF; DECYL GLUCOSIDE

Tazza Hand Sanitizing Wipes

Drug Facts

Active ingredient

Benzalkonium Chloride 0.13%

Purpose

Antimicrobial

Uses

- for hand sanitizing to decrease bacteria on the skin
- recommended for repeated use

Warnings

For external use only

When using this product avoid contact with eyes. In case of eye contact, flush eyes with water.

Stop use and ask a doctor if irritation or redness develop

Keep out of reach of children. If swallowed, get medical help or contact a Poison Control Center right away.

Directions

- take wipe and rub thoroughly over all surfaces of both hands
- rub hands together briskly to dry
- dispose of wipe

INACTIVE INGREDIENT

Inactive ingredients Purified Water, Glycerin, Aloe Barbadensis Leaf Juice, Decyl Glucoside

Manufactured for Terraboost Media, LLC
3109 Grand Avenue #300, Miami, DL 33133

Questions? Tazza Brands:

877-837-7210

www.tazzabrands.com

MADE IN USA

PACKAGE LABEL

tazza®

ANTISEPTIC

HAND SANITIZING WIPES

Contains Benzalkonium Chloride

Alcohol-Free Formula

Kills 99.99% of most common germs

1200 Wet Wipes

4.25" x 6.75" (10.8 cm x 17.2 cm)